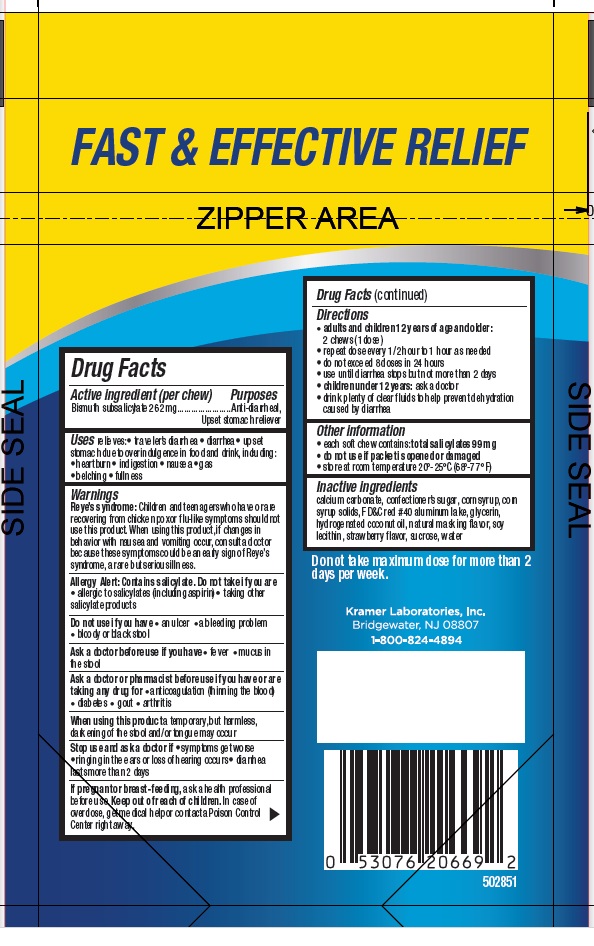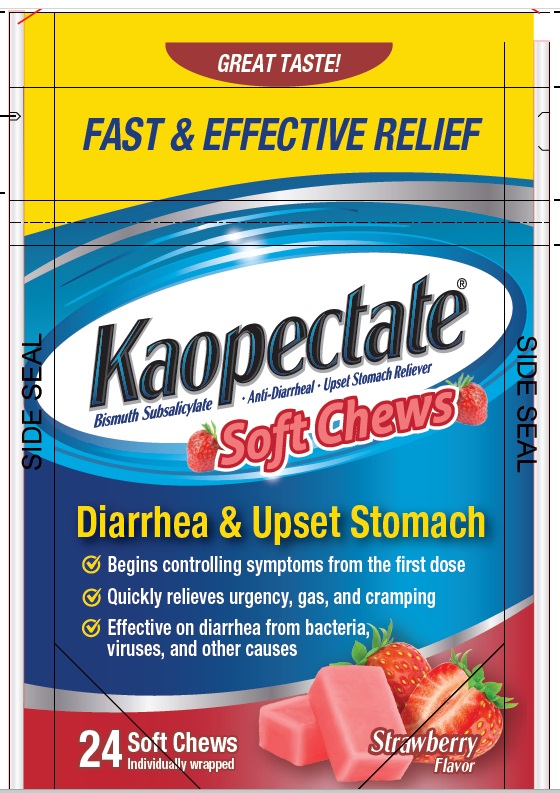 DRUG LABEL: Kaopectate
NDC: 55505-206 | Form: TABLET, CHEWABLE
Manufacturer: Kramer Laboratories
Category: otc | Type: HUMAN OTC DRUG LABEL
Date: 20251219

ACTIVE INGREDIENTS: Bismuth Subsalicylate 262 mg/1 1
INACTIVE INGREDIENTS: Calcium Carbonate; Sucrose; Corn Syrup; Fd&C Red No. 40; Glycerin; Hydrogenated Coconut Oil; Lecithin, Soybean; Water

Drug Facts

ACTIVE INGREDIENT

Active ingredient (per chew) | Purposes
Bismuth subsalicylate 262 mg | Anti-diarrheal, Upset stomach reliever

INDICATIONS AND USAGE

Uses relieves:

- traveler’s diarrhea
- diarrhea
- upset stomach due to overindulgence in food and drink, including:
  - heartburn
  - indigestion
  - nausea
  - gas
  - belching
  - fullness

Warnings

Reye’s syndrome: Children and teenagers who have or are recovering from chicken pox or flu-like symptoms should not use this product. When using this product, if changes in behavior with nausea and vomiting occur, consult a doctor because these symptoms could be an early sign of Reye’s syndrome, a rare but serious illness.

Allergy Alert: Contains salicylate.

Do not take if you are

- allergic to salicylates (including aspirin)
- taking other salicylate products

Do not use if you have

- an ulcer
- a bleeding problem
- bloody or black stool

Ask a doctor before use if you have

- fever
- mucus in the stool

Ask a doctor or pharmacist before use if you are taking any drug for

- anticoagulation (thinning the blood)
- diabetes
- gout
- arthritis

When using this product a temporary, but harmless, darkening of the stool and/or tongue may occur

Stop use and ask a doctor if

- symptoms get worse
- ringing in the ears or loss of hearing occurs
- diarrhea lasts more than 2 days

PREGNANCY OR BREAST FEEDING

If pregnant or breast-feeding, ask a health professional before use.

Keep out of reach of children. In case of overdose, get medical help or contact a Poison Control Center right away.

Directions

- adults and children 12 years of age and older: 2 chews (1 dose)
- repeat dose every 1/2 hour to 1 hour as needed
- do not exceed 8 doses in 24 hours
- use until diarrhea stops but not more than 2 days
- children under 12 years: ask a doctor
- drink plenty of clear fluids to help prevent dehydration caused by diarrhea

Other information

- each soft chew contains: total salicylates 99 mg
- do not use if carton was opened or if printed foil inner seal under bottle cap is torn or missing
- store at room temperature 20º-25º C (68º-77º F)

Inactive ingredients

calcium carbonate, confectioner’s sugar, corn syrup, corn syrup solids, FD&C red #40 aluminum lake, glycerin, hydrogenated coconut oil, natural masking flavor, soy lecithin, strawberry flavor, sucrose, water

PRINCIPAL DISPLAY PANEL

GREAT TASTE!
FAST & EFFECTIVE RELIEF
Kaopectate®
Bismuth Subsalicylate • Anti-Diarrheal • Upset Stomach Reliever
Soft Chews
Diarrhea & Upset Stomach
✓ Begins controlling symptoms from the first dose
✓ Quickly relieves urgency, gas, and cramping
✓ Effective on diarrhea from bacteria, viruses, and other causes
24 Soft Chews
Individually wrapped
Strawberry Flavor

FAST & EFFECTIVE RELIEF
Do not take maximum dose for more than 2 days per week.
Kramer Laboratories, Inc.
Bridgewater, NJ 08807
1-800-824-4894
502851